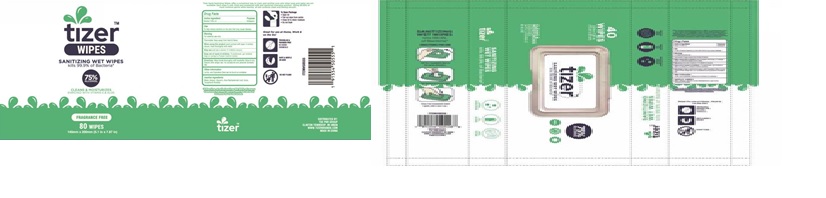 DRUG LABEL: Tizer Sanitizing Wet Wipes
NDC: 71611-060 | Form: CLOTH
Manufacturer: CLICK PRODUCTS LLC
Category: otc | Type: HUMAN OTC DRUG LABEL
Date: 20200907

ACTIVE INGREDIENTS: ALCOHOL 75 1/100 1
INACTIVE INGREDIENTS: .ALPHA.-TOCOPHEROL ACETATE; GLYCERIN; ALOE VERA LEAF; WATER

Tizer Sanitizing Wet Wipes

Active Ingredient(s)

Ethyl Alcohol 75%

Purpose

Antiseptic

Use

For hand washing to decrease bacteria on the skin

Warnings

For external use only
Do not use in the eyes

- Do not use in the eyes

WHEN USING

/

STOP USE

irritation and redness develop
condition persists for more than 72 hours

Keep out of reach of children. If swallowed, get medical help or contact a Poison Control Center right away.

Directions

wet hands thoroughly with product and allow to dry without wiping

Other information

/

Inactive ingredients

Water, Glycerin, Aloe vera leaf juice, Tocopheryl acetate